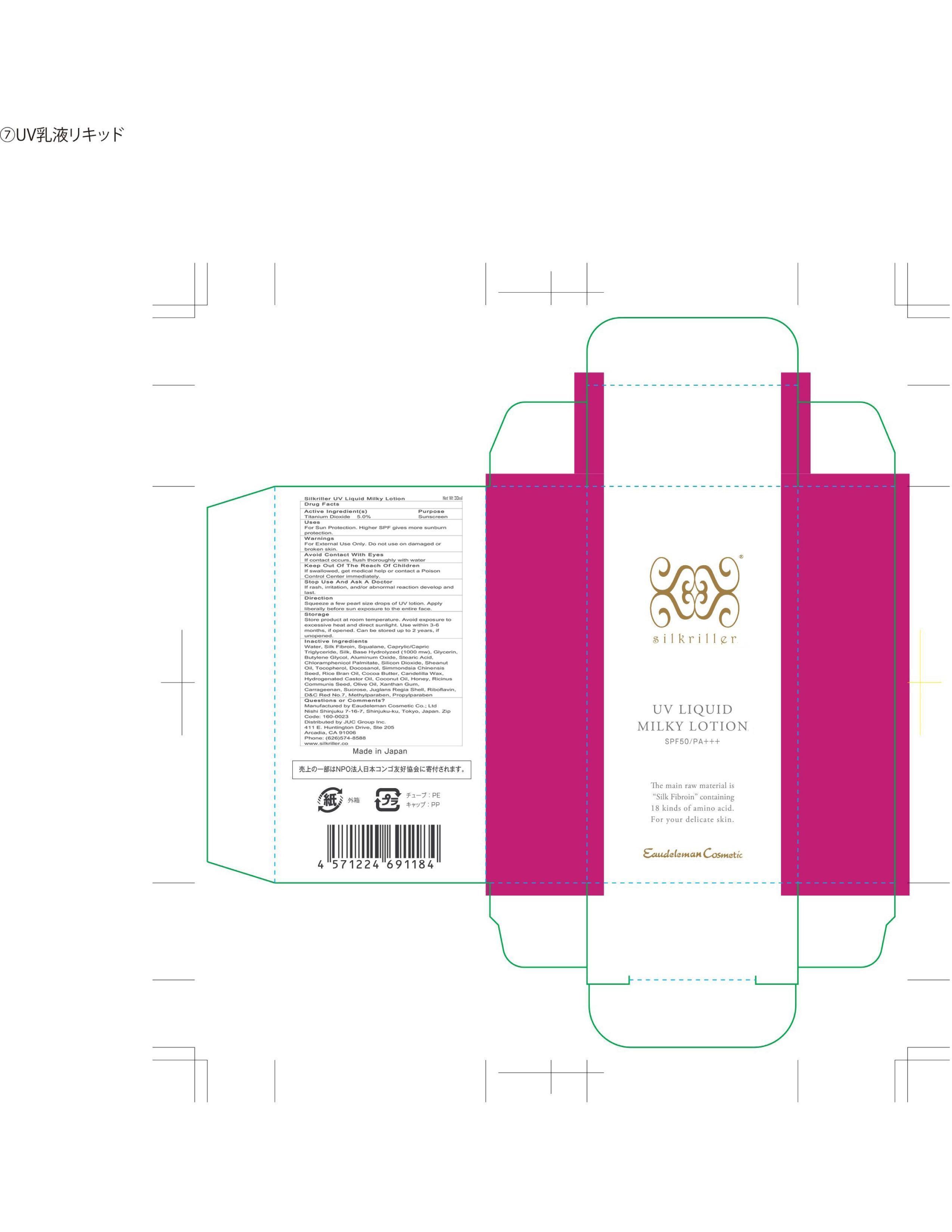 DRUG LABEL: Eaudeleman Cosmetic UV Liquid
NDC: 69893-301 | Form: LOTION
Manufacturer: Eaudeleman Cosmetic Co Ltd
Category: otc | Type: HUMAN OTC DRUG LABEL
Date: 20151104

ACTIVE INGREDIENTS: TITANIUM DIOXIDE 5 g/100 g
INACTIVE INGREDIENTS: WATER; SILK FIBROIN; SQUALANE; CAPRYLIC/CAPRIC ACID; SILK, BASE HYDROLYZED (1000 MW); GLYCERIN; BUTYLENE GLYCOL; ALUMINUM OXIDE; STEARIC ACID; CHLORAMPHENICOL PALMITATE; SILICON DIOXIDE; SHEANUT OIL; TOCOPHEROL; DOCOSANOL; SIMMONDSIA CHINENSIS SEED; RICE BRAN OIL; COCOA BUTTER; CANDELILLA WAX; HYDROGENATED CASTOR OIL; COCONUT OIL; HONEY; RICINUS COMMUNIS SEED; OLIVE OIL; XANTHAN GUM; CARRAGEENAN; SUCROSE; JUGLANS REGIA SHELL; RIBOFLAVIN; D&C RED NO. 7; METHYLPARABEN; PROPYLPARABEN

Eaudeleman Cosmetic

ACTIVE INGREDIENT

Titanium Dioxide 5.0%

PURPOSE

Titanium Dioxide Sunscreen

Indications and Usage

Helps prevent sunburn.

Higher SPF gives more sunburn protection.

Directions

Squeeze out a few drops of UV lotion the size of a pearl. Apply liberally before sun exposure to the entire face.

Warnings

For external use only. Do not use on damaged or broken skin.

Keep Out of Reach of Children.

If swallowed, get medical help or contact a Poison Control Center immediately.

Avoid Contact With Eyes.

If contact occurs, flush thoroughly with water.

STOP USE AND ASK A DOCTOR IF

Rash, irritation and/or abnormal reaction develop and last.

Storage

Store product at room temperature. Avoid exposure to excessive heat and direct sunlight. Use within 3-6 months if opened. Can be stored up to 2 years if unopened.

Questions or Comments?

Manufactured by Eaudeleman Cosmetic

Nishi Shinjuku 7-16-7, Shinjuku-ku, Tokyo 160-0023

Made in Japan

Distributed by JUC Group Inc.

411 East Huntington Drive, Suite 205

Arcadia, CA 91006

(626)574-8588

www.silkriller.com

INACTIVE INGREDIENTS

WATER, SILK FIBROIN, SQUALANE, CAPRYLIC/CAPRIC TRIGLYCERIDE, SILK, BASE HYDROLYZED (1000 MW), GLYCERIN, BUTYLENE GLYCOL, ALUMINUM OXIDE, STEARIC ACID, CHLORAMPHENICOL PALMITATE, SILICON DIOXIDE, SHEANUT OIL, TOCOPHEROL, DOCOSANOL, SIMMONDSIA CHINENSIS SEED, RICE BRAN OIL, COCOA BUTTER, CANDELILLA WAX, HYDROGENATED CASTOR OIL, COCONUT OIL, HONEY, RICINUS COMMUNIS SEED, OLIVE OIL, XANTHAN GUM, CARRAGEENAN, SUCROSE, JUGLANS REGIA SHELL, RIBOFLAVIN, D&C RED NO.7, METHYLPARABEN, PROPYLPARABEN